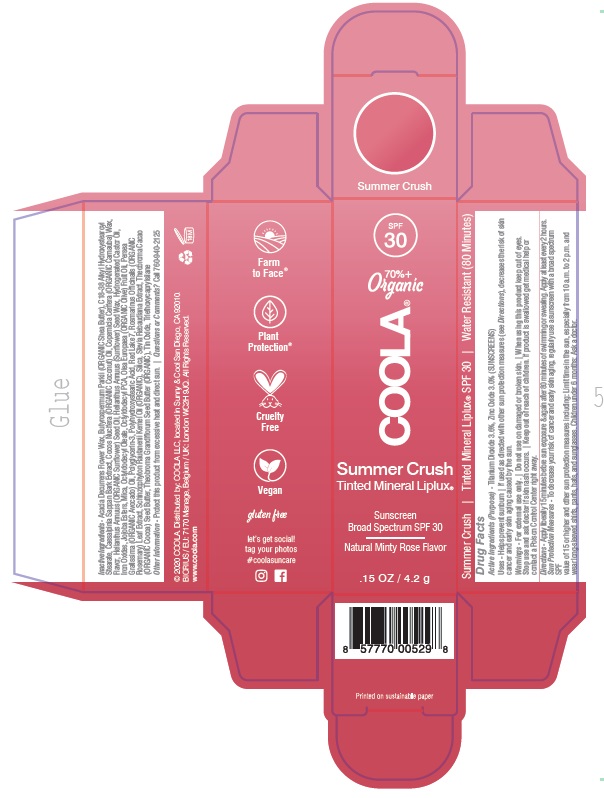 DRUG LABEL: COOLA Mineral Liplux Lip Balm SPF 30 Summer Crush
NDC: 79753-057 | Form: STICK
Manufacturer: COOLA, LLC
Category: otc | Type: HUMAN OTC DRUG LABEL
Date: 20240202

ACTIVE INGREDIENTS: TITANIUM DIOXIDE 3.6 g/100 g; ZINC OXIDE 3 g/100 g
INACTIVE INGREDIENTS: SCHINZIOPHYTON RAUTANENII SEED OIL; OCTYLDODECYL OLEATE; THEOBROMA GRANDIFLORUM SEED BUTTER; STANNIC OXIDE; POLYHYDROXYSTEARIC ACID (2300 MW); OLIVE OIL; D&C RED NO. 7; HYDROGENATED CASTOR OIL; OCTYLDODECYL PCA; FERRIC OXIDE RED; COCONUT OIL; CARNAUBA WAX; AVOCADO OIL; COCOA BUTTER; HELIANTHUS ANNUUS SEED WAX; ACACIA DECURRENS FLOWER WAX; POLYGLYCERIN-3; CAESALPINIA SAPPAN BARK; MICA; ROSEMARY; SHEA BUTTER; JOJOBA OIL, RANDOMIZED; SUNFLOWER OIL; C18-38 ALKYL HYDROXYSTEAROYL STEARATE; STEVIA REBAUDIANA WHOLE; TRIETHOXYCAPRYLYLSILANE; SILICON DIOXIDE

COOLA Mineral Liplux Lip Balm SPF 30 - Summer Crush

ACTIVE INGREDIENT

Titanium Dioxide 3.6%

Zinc Oxide 3.0%

PURPOSE

Sunscreen

Uses

- Helps prevent sunburn
- If used as directed with other sun protection measures (see Directions), decreases the risk of skin cancer and early skin aging caused by the sun.

WARNINGS

- For external use only.
- Do not use on damaged or broken skin.
- When using this product keep out of eyes.
- Stop use and ask doctor if skin rash occurs

Keep out of reach of children. If product is swallowed get medical help or contact a Poison Control Center right away.

Directions

- Apply liberally 15 minutes before sun exposure & again after 80 minutes of swimming or sweating.
- Apply at least every 2 hours.
- Sun Protection Measures - To decrease your risk of cancer and early skin aging, regularly use a sunscreen with a broad spectrum SPF value of 15 or higher and other sun protection measures including: Limit time in the sun, especially from 10 a.m. to 2 p.m. and wear long-sleeved shirts, pants, hats, and sunglasses.

INACTIVE INGREDIENT

Acacia Decurrens Flower Wax, Butyrospermum Parkii (ORGANIC Shea Butter), C18-38 Alkyl Hydroxystearoyl
Stearate, Caesalpinia Sappan Bark Extract, Cocos Nucifera (ORGANIC Coconut) Oil, Copernicia Cerifera (ORGANIC Carnauba) Wax,
Flavor, Helianthus Annuus (ORGANIC Sunflower) Seed Oil, Helianthus Annuus (Sunflower) Seed Wax, Hydrogenated Castor Oil,
Iron Oxides, Jojoba Esters, Mica, Octyldodecyl Oleate, Octyldodecyl PCA, Olea Europaea (ORGANIC Olive) Fruit Oil, Persea
Gratissima (ORGANIC Avocado) Oil, Polyglycerin-3, Polyhydroxystearic Acid, Red Lake 7, Rosmarinus Officinalis (ORGANIC
Rosemary) Leaf Extract, Schinziophyton Rautanenii Kernel Oil (ORGANIC), Silica, Stevia Rebaudiana Extract, Theobroma Cacao
(ORGANIC Cocoa) Seed Butter, Theobroma Grandiflorum Seed Butter (ORGANIC), Tin Oxide, Triethoxycaprylsilane

OTHER SAFETY INFORMATION

Protect this product from excessive heat and direct sun.

QUESTIONS

Call 760-940-2125